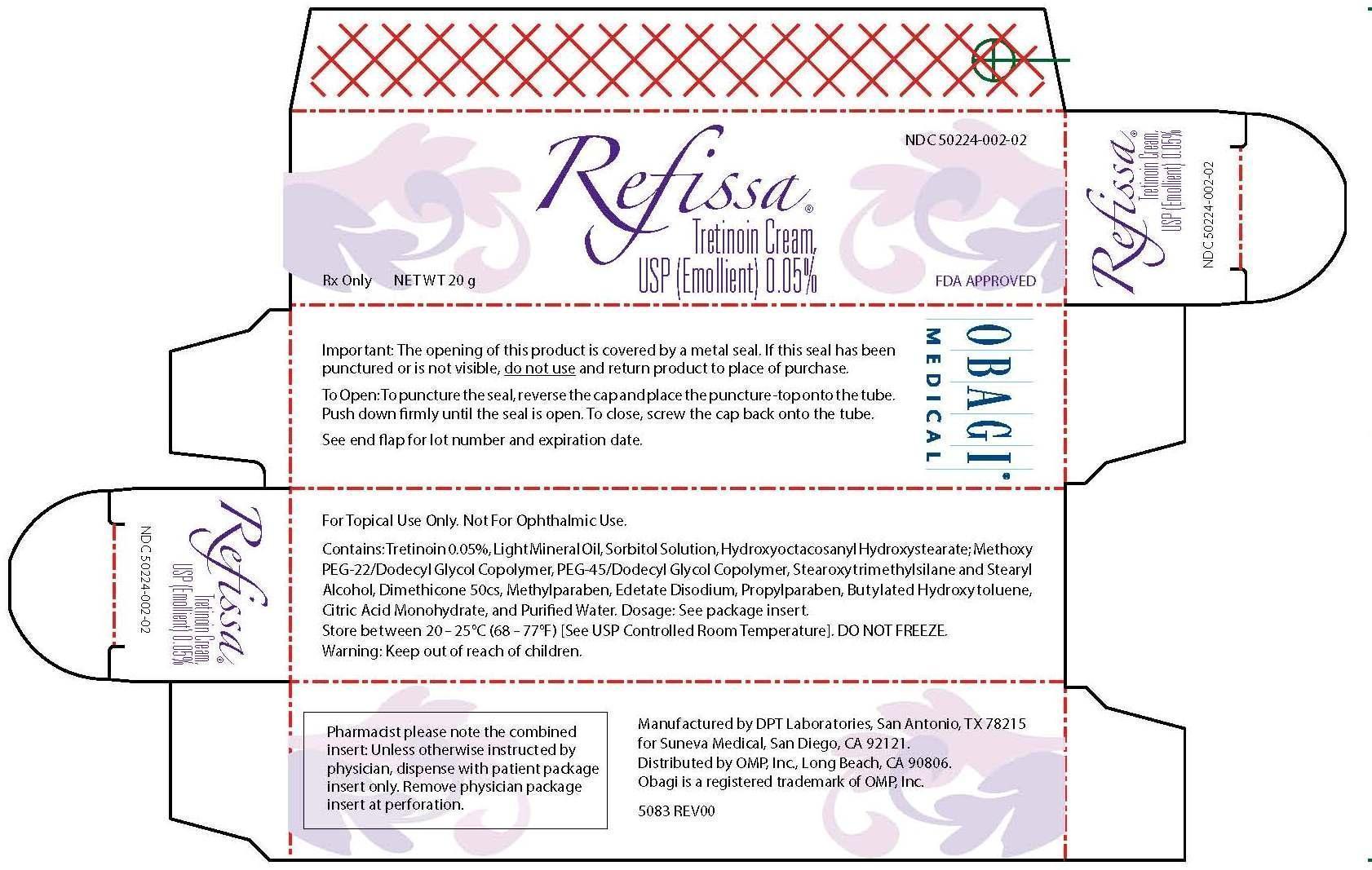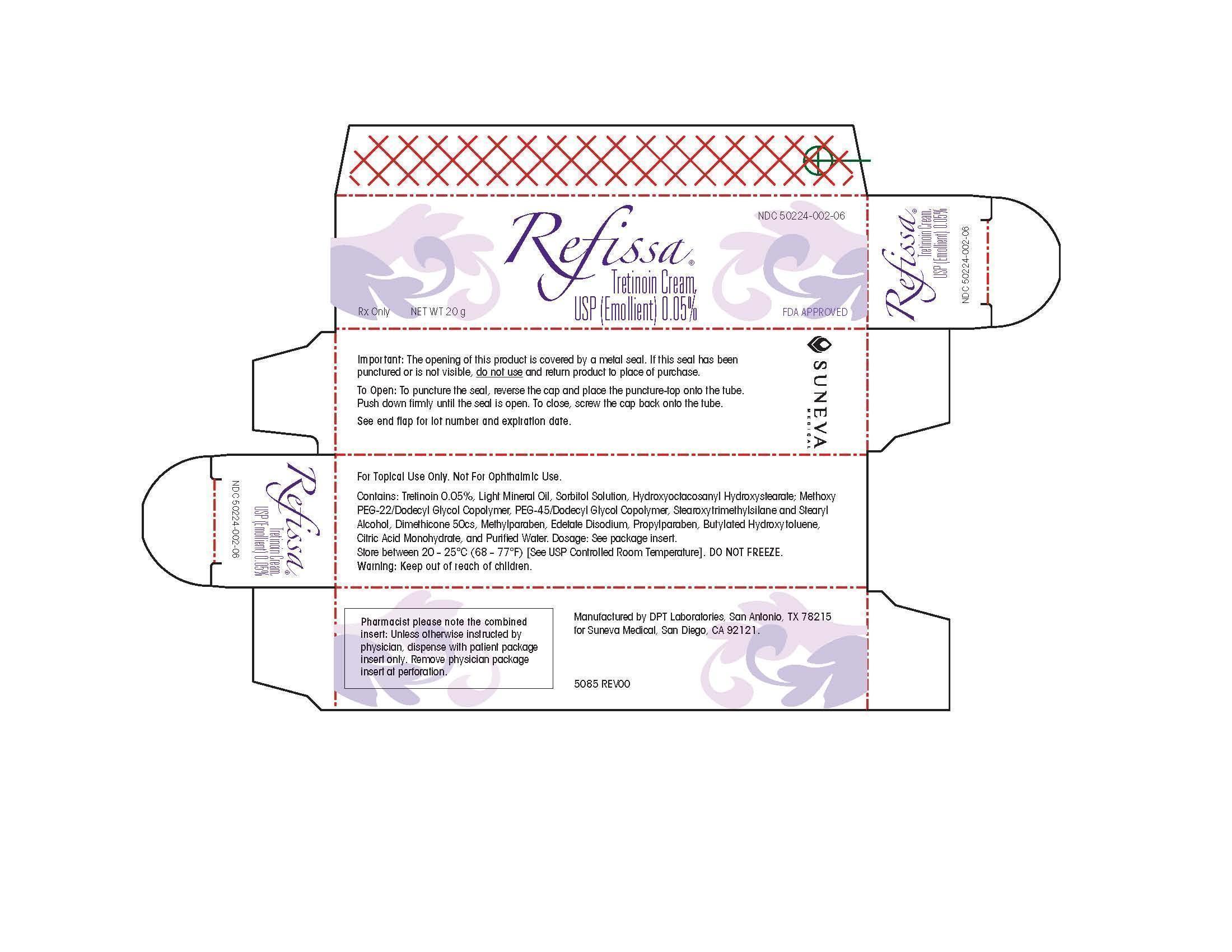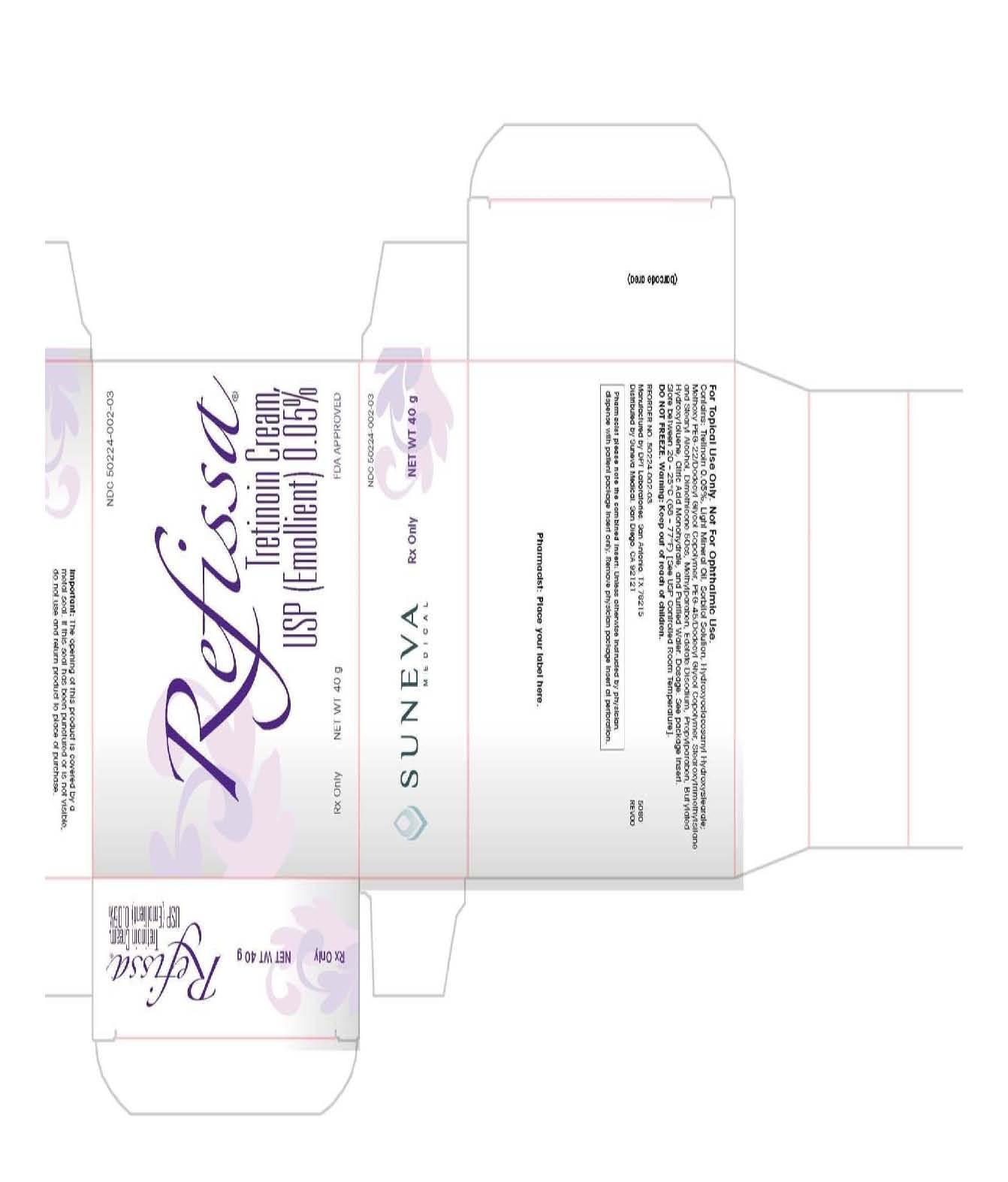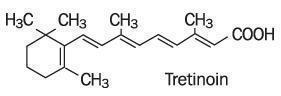 DRUG LABEL: REFISSA
NDC: 50224-002 | Form: CREAM
Manufacturer: Suneva Medical, Inc.
Category: prescription | Type: HUMAN PRESCRIPTION DRUG LABEL
Date: 20140108

ACTIVE INGREDIENTS: TRETINOIN 0.5 mg/1 g
INACTIVE INGREDIENTS: BUTYLATED HYDROXYTOLUENE; CITRIC ACID MONOHYDRATE; EDETATE DISODIUM; LIGHT MINERAL OIL; DIMETHICONE; METHYLPARABEN; PROPYLPARABEN; WATER; SORBITOL

FOR TOPICAL USE ON THE FACE ONLY

DESCRIPTION

Refissa [Tretinoin Cream, USP (Emollient) 0.05%], contains the active ingredient tretinoin (a retinoid) in an emollient cream base. Tretinoin is a yellow-to-light-orange crystalline powder having a characteristic floral odor. Tretinoin is soluble in dimethylsulfoxide, slightly soluble in polyethylene glycol 400, octanol, and 100% ethanol. It is practically insoluble in water and mineral oil, and it is insoluble in glycerin. The chemical name for tretinoin is (all-E)-3,7-dimethyl-9-(2,6,6-trimethyl-1-cyclonexen-1-yl)-2,4,6,8-nonatetraenoic acid. Tretinoin is also referred to as all-trans-retinoic acid and has a molecular weight of 300.44. The structural formula is represented below.

Refissa contains tretinoin at a concentration of 0.05% w/w in a water-in-oil emulsion formulation consisting of light mineral oil, sorbitol solution, hydroxyoctacosanyl hydroxystearate; methoxy PEG-22/dodecyl glycol copolymer, PEG-45/dodecyl glycol copolymer, stearoxytrimethylsilane and stearyl alcohol, dimethicone 50 cs, methylparaben, edetate disodium, propylparaben, butylated hydroxytoluene, citric acid monohydrate, and purified water.

CLINICAL PHARMACOLOGY

The exact mechanism of action of tretinoin is unknown although retinoids are believed to exert an effect on the growth and differentiation of various epithelial cells. When applied topically, however, there was no noted increase in desmosine, hydroxyproline, or elastin mRNA in human skin. In addition, the role of the irritative nature of this product in effecting the positive effects attributed to this product for its indication has not yet been fully determined.

The transdermal absorption of tretinoin from various topical formulations ranged from 1% to 31% of applied dose, depending on whether it was applied to healthy skin or dermatitic skin. When percutaneous absorption of Tretinoin Cream, USP (Emollient) 0.05% was assessed in healthy male subjects (n=14) after a single application, as well as after repeated daily applications for 28 days, the absorption of tretinoin was less than 2% and endogenous concentrations of tretinoin and its major metabolites were unaltered.

INDICATIONS AND USAGE

(To understand fully the indication for this product, please read the entire INDICATIONS AND USAGE section of the labeling.)

Refissa [Tretinoin Cream, USP (Emollient) 0.05%] is indicated as an adjunctive agent (see second bullet point below) for use in the mitigation (palliation) of fine wrinkles, mottled hyperpigmentation, and tactile roughness of facial skin in patients who do not achieve such palliation using comprehensive skin care and sun avoidance programs (see bullet 3 for populations in which effectiveness has not been established). REFISSA DOES NOT ELIMINATE WRINKLES, REPAIR SUN-DAMAGED SKIN, REVERSE PHOTOAGING, or RESTORE A MORE YOUTHFUL or YOUNGER DERMAL HISTOLOGIC PATTERN. Many patients achieve desired palliative effects on fine wrinkling, mottled hyperpigmentation, and tactile roughness of facial skin with the use of comprehensive skin care and sun avoidance programs including sunscreens, protective clothing, and emollient creams NOT containing tretinoin.

- Tretinoin Cream, USP (Emollient) 0.05% has demonstrated NO MITIGATING EFFECT on significant signs of chronic sun exposure such as coarse or deep wrinkling, skin yellowing, lentigines, telangiectasia, skin laxity, keratinocytic atypia, melanocytic atypia, or dermal elastosis.
- Refissa should be used under medical supervision as an adjunct to a comprehensive skin care and sun avoidance program that includes the use of effective sunscreens (minimum SPF of 15) and protective clothing when desired results on fine wrinkles, mottled hyperpigmentation, and roughness of facial skin have not been achieved with a comprehensive skin care and sun avoidance program alone.
- The effectiveness of Refissa [Tretinoin Cream, USP (Emollient) 0.05%] in the mitigation of fine wrinkles, mottled hyperpigmentation, and tactile roughness of facial skin has not been established in people greater than 50 years of age OR in people with moderately to heavily pigmented skin. In addition, patients with visible actinic keratoses and patients with a history of skin cancer were excluded from clinical trials of Tretinoin Cream, USP (Emollient) 0.05%. Thus the effectiveness and safety of Refissa in these populations are not known at this time.
- Neither the safety nor the effectiveness of Tretinoin Cream, USP (Emollient) for the prevention or treatment of actinic keratoses or skin neoplasms has been established.
- Neither the safety nor the efficacy of using Tretinoin Cream, USP (Emollient) 0.05% daily for greater than 48 weeks has been established, and daily use beyond 48 weeks has not been systematically and histologically investigated in adequate and well-controlled trials. (See WARNINGS section.)

CLINICAL TRIALS DATA

Two adequate and well-controlled trials were conducted involving a total of 161 evaluable patients (under 50 years of age) treated with Tretinoin Cream, USP (Emollient) 0.05% and 154 evaluable patients treated with the vehicle emollient cream on the face for 24 weeks as an adjunct to a comprehensive skin care and sun avoidance program, to assess the effects on fine wrinkling, mottled hyperpigmentation, and tactile skin roughness. Patients were evaluated at baseline on a 10-point scale, and changes from that baseline rating were categorized as follows:

No Improvement: No change or an increase of 1 unit or more
Minimal Improvement: Reduction of 1 unit
Moderate Improvement: Reduction of 2 units or more

In these trials, the fine wrinkles, mottled hyperpigmentation, and tactile roughness of the facial skin were thought to be caused by multiple factors which included intrinsic aging or environmental factors, such as chronic sun exposure.

The results of these assessments are as follows:

FINE WRINKLING
 | NO IMPROVEMENT | MINIMAL IMPROVEMENT | MODERATE IMPROVEMENT
Tretinoin Cream, USP (Emollient) 0.05% + CSP* | 36% | 40% | 24%
Vehicle + CSP | 62% | 30% | 8%
MOTTLED HYPERPIGMENTATION
 | NO IMPROVEMENT | MINIMAL IMPROVEMENT | MODERATE IMPROVEMENT
Tretinoin Cream, USP (Emollient) 0.05% + CSP* | 35% | 27% | 38%
Vehicle + CSP | 53% | 21% | 27%
TACTILE SKIN ROUGHNESS
 | NO IMPROVEMENT | MINIMAL IMPROVEMENT | MODERATE IMPROVEMENT
Tretinoin Cream, USP (Emollient) 0.05% + CSP* | 49% | 35% | 16%
Vehicle + CSP | 67% | 23% | 10%
*CSP= Comprehensive skin protection and sun avoidance programs included use of sunscreens, protective clothing, and emollient cream.

Most of the improvement in these signs was noted during the first 24 weeks of therapy. Thereafter, therapy primarily maintained the improvement realized during the first 24 weeks.

A majority of patients will lose most mitigating effects of Refissa on fine wrinkles, mottled hyperpigmentation, and tactile roughness of facial skin with discontinuation of a comprehensive skin care and sun avoidance program including Refissa; however, the safety and effectiveness of using Refissa daily for greater than 48 weeks have not been established.

CONTRAINDICATIONS

This drug is contraindicated in individuals with a history of sensitivity reactions to any of its components. It should be discontinued if hypersensitivity to any of its ingredients is noted.

WARNINGS

- Refissa [Tretinoin Cream, USP (Emollient) 0.05%] is a dermal irritant, and the results of continued irritation of the skin for greater than 48 weeks in chronic long-term use are not known. There is evidence of atypical changes in melanocytes and keratinocytes, and of increased dermal elastosis in some patients treated with Tretinoin Cream, USP (Emollient) 0.05% for longer than 48 weeks. The significance of these findings is unknown.
- Safety and effectiveness of Refissa in individuals with moderately or heavily pigmented skin have not been established.
- Refissa should not be administered if the patient is also taking drugs known to be photosensitizers (e.g., thiazides, tetracyclines, fluoroquinolones, phenothiazines, sulfonamides) because of the possibility of augmented phototoxicity.

Because of heightened burning susceptibility, exposure to sunlight (including sunlamps) should be avoided or minimized during use of Refissa. Patients must be warned to use sunscreens (minimum SPF of 15) and protective clothing when using Refissa. Patients with sunburn should be advised not to use Refissa until fully recovered. Patients who may have considerable sun exposure, e.g., due to their occupation and those patients with inherent sensitivity to sunlight, should exercise particular caution when using Refissa and assure that the precautions outlined in the Patient Package Insert are observed.

Tretinoin should be kept out of the eyes, mouth, angles of the nose, and mucous membranes. Topical use may cause severe local erythema, pruritus, burning, stinging, and peeling at the site of application. If the degree of local irritation warrants, patients should be directed to use less medication, decrease the frequency of application, discontinue use temporarily, or discontinue use altogether.

Tretinoin has been reported to cause severe irritation on eczematous skin and should be used only with caution in patients with this condition.

Application of larger amounts of medication than recommended will not lead to more rapid or better results, and marked redness, peeling, or discomfort may occur.

PRECAUTIONS

General

Refissa [Tretinoin Cream, USP (Emollient) 0.05%] should only be used as an adjunct to a comprehensive skin care and sun avoidance program. (See INDICATIONS AND USAGE section.)

If a drug sensitivity, chemical irritation, or a systemic adverse reaction develops, use of Refissa should be discontinued.

Weather extremes, such as wind or cold, may be more irritating to patients using Refissa.

Information for Patients

See Patient Package Insert.

Drug Interactions

Concomitant topical medications, medicated or abrasive soaps, shampoos, cleansers, cosmetics with a strong drying effect, products with high concentrations of alcohol, astringents, spices or lime, permanent wave solutions, electrolysis, hair depilatories or waxes, and products that may irritate the skin should be used with caution in patients being treated with Refissa [Tretinoin Cream, USP (Emollient) 0.05%] because they may increase irritation with Refissa.

Refissa should not be administered if the patient is also taking drugs known to be photosensitizers (e.g., thiazides, tetracyclines, fluoroquinolones, phenothiazines, sulfonamides) because of the possibility of augmented phototoxicity.

Carcinogenesis, Mutagenesis, Impairment of Fertility

In a lifetime dermal study in CD-1 mice at 100 and 200 times the average recommended human topical clinical dose, a few skin tumors in the female mice and liver tumors in male mice were observed. The biological significance of these findings is not clear because they occurred at doses that exceeded the dermal maximally tolerated dose (MTD) of tretinoin and because they were within the background natural occurrence rate for these tumors in this strain of mice. There was no evidence of carcinogenic potential when tretinoin was administered topically at a dose 5 times the average recommended human topical clinical dose. For purposes of comparisons of the animal exposure to the human exposure, the “recommended human topical clinical dose” is defined as 500 mg of Refissa applied daily to a 50 kg person.

In a chronic, two-year bioassay of Vitamin A acid in mice performed by Tsubura and Yamamoto, generalized amyloid deposition was reported in all groups in the basal layer of the Vitamin A treated skin. In CD-1 mice, a similar study reported hyalinization of the treated skin sites and the incidence of this finding was 0/50, 3/50, and 2/50 in male mice and 1/50, 0/50, 4/50 and 2/50 in female mice from the vehicle control, 0.25 mg/kg, 0.5 mg/kg, and 1 mg/kg groups, respectively.

Studies in hairless albino mice suggest that tretinoin may enhance the tumorigenic potential of carcinogenic doses of UVB and UVA light from a solar simulator. In other studies, when lightly pigmented hairless mice treated with tretinoin were exposed to carcinogenic doses of UVB light, the incidence and rate of development of skin tumors were either reduced or no effect was seen. Due to significantly different experimental conditions, no strict comparison of these disparate data is possible at this time. Although the significance of these studies in humans is not clear, patients should minimize exposure to sun.

The mutagenic potential of tretinoin was evaluated in the Ames assay and in the in vivo mouse micronucleus assay, both of which were negative.

Dermal Segment l and III studies with Tretinoin Cream, USP (Emollient) 0.05% have not been performed in any species. In oral Segment I and Segment III studies in rats with tretinoin, decreased survival of neonates and growth retardation were observed at doses in excess of 2 mg/kg/day (>400 times the average human topical clinical dose).

Pregnancy

Teratogenic effects: Pregnancy Category C.

ORAL tretinoin has been shown to be teratogenic in rats, mice, rabbits, hamsters, and subhuman primates. It was teratogenic and fetotoxic in rats when given orally or topically in doses 1000 times the average recommended human topical clinical dose. However, variations in teratogenic doses among various strains of rats have been reported. In the cynomolgus monkey, which, metabolically, is closer to humans for tretinoin than the other species examined, fetal malformations were reported at doses of 10 mg/kg/day or greater, but none were observed at 5 mg/kg/day (1000 times the average recommended human topical clinical dose), although increased skeletal variations were observed at all doses. A dose-related increase in embryolethality and abortion was reported. Similar results have also been reported in pigtail macaques.

TOPICAL tretinoin in animal teratogenicity tests has generated equivocal results. There is evidence for teratogenicity (shortened or kinked tail) of topical tretinoin in Wistar rats at doses greater than 1 mg/kg/day (200 times the recommended human topical clinical dose). Anomalies (humerus: short 13%, bent 6%, os parietal incompletely ossified 14%) have also been reported when 10 mg/kg/day was dermally applied.

There are other reports in New Zealand White rabbits administered with doses of approximately 80 times the recommended human topical clinical dose of an increased incidence of domed head and hydrocephaly, typical of retinoid-induced fetal malformations in this species.

In contrast, several well-controlled animal studies have shown that dermally applied tretinoin was not teratogenic, at doses of 100 and 200 times the recommended human topical clinical dose, in rats and rabbits, respectively.

With widespread use of any drug, a small number of birth defect reports associated temporally with the administration of the drug would be expected by chance alone. Thirty cases of temporally-associated congenital malformations have been reported during two decades of clinical use of another formulation of topical tretinoin (Retin-A). Although no definite pattern of teratogenicity and no causal association has been established from these cases, 5 of the reports describe the rare birth defect category holoprosencephaly (defects associated with incomplete midline development of the forebrain). The significance of these spontaneous reports in terms of risk to the fetus is not known.

Non-teratogenic effects

Dermal tretinoin has been shown to be fetotoxic in rabbits when administered in doses 100 times the recommended topical human clinical dose. Oral tretinoin has been shown to be fetotoxic in rats when administered in doses 500 times the recommended topical human clinical dose.

There are, however, no adequate and well-controlled studies in pregnant women. Refissa [Tretinoin Cream, USP (Emollient) 0.05%] should not be used during pregnancy.

Nursing Mothers

It is not known whether this drug is excreted in human milk. Because many drugs are excreted in human milk, caution should be exercised when Refissa is administered to a nursing woman.

Pediatric Use

Safety and effectiveness in patients less than 18 years of age have not been established.

Geriatric Use

Safety and effectiveness in individuals older than 50 years of age have not been established.

ADVERSE REACTIONS

(See WARNINGS and PRECAUTIONS sections.)

In double-blind, vehicle-controlled studies involving 179 patients who applied Tretinoin Cream, USP (Emollient) 0.05% to their faces, adverse reactions associated with the use of Tretinoin Cream, USP (Emollient) 0.05% were limited primarily to the skin. During these trials, 4% of patients had to discontinue use of Tretinoin Cream, USP (Emollient) 0.05% because of adverse reactions. These discontinuations were due to skin irritation or related cutaneous adverse reactions.

Local reactions such as peeling, dry skin, burning, stinging, erythema, and pruritus were reported by almost all subjects during therapy with Tretinoin Cream, USP (Emollient) 0.05%. These signs and symptoms were usually of mild to moderate severity and generally occurred early in therapy. In most patients the dryness, peeling, and redness recurred after an initial (24 week) decline.

OVERDOSAGE

Application of larger amounts of medication than recommended has not been shown to lead to more rapid or better results, and marked redness, peeling, or discomfort may occur. Oral ingestion of the drug may lead to the same side effects as those associated with excessive oral intake of Vitamin A.

DOSAGE AND ADMINISTRATION

- Do NOT use Refissa [Tretinoin Cream, USP (Emollient) 0.05%] if the patient is pregnant or is attempting to become pregnant or is at high risk of pregnancy
- Do NOT use Refissa if the patient is sunburned or if the patient has eczema or other chronic skin condition(s)
- Do NOT use Refissa if the patient is inherently sensitive to sunlight
- Do NOT use Refissa if the patient is also taking drugs known to be photosensitizers (e.g., thiazides, tetracyclines, fluoroquinolones, phenothiazines, sulfonamides) because of the possibility of augmented phototoxicity.

Patients require detailed instruction to obtain maximal benefits and to understand all the precautions necessary to use this product with greatest safety. The physician should review the Patient Package Insert.

Refissa should be applied to the face once a day before retiring, using only enough to cover the entire affected area lightly. Patients should gently wash their faces with a mild soap, pat the skin dry, and wait 20 to 30 minutes before applying Refissa. The patient should apply a pea-sized amount of cream to cover the entire face lightly. Special caution should be taken when applying the cream to avoid the eyes, ears, nostrils, and mouth.

Application of Refissa [Tretinoin Cream, USP (Emollient) 0.05%] may cause a transitory feeling of warmth or slight stinging.

Mitigation (palliation) of facial fine wrinkling, mottled hyperpigmentation, and tactile roughness may occur gradually over the course of therapy. Up to six months of therapy may be required before the effects are seen. Most of the improvement noted with Refissa is seen during the first 24 weeks of therapy. Thereafter, therapy primarily maintains the improvement realized during the first 24 weeks.

With discontinuation of Refissa therapy, a majority of patients will lose most mitigating effects of Refissa on fine wrinkles, mottled hyperpigmentation, and tactile roughness of facial skin; however, the safety and effectiveness of using Refissa daily for greater than 48 weeks have not been established.

Application of larger amounts of medication than recommended may not lead to more rapid results or better results, and marked redness, peeling, or discomfort may occur.

Patients treated with Refissa may use cosmetics, but the areas to be treated should be cleansed thoroughly before the medication is applied. (See PRECAUTIONS section.)

HOW SUPPLIED

Refissa is available in the following:

40 g tubes NDC 50224-002-03

20 g tubes NDC 50224-002-06

20 g tubes NDC 50224-002-02 Obagi Medical

Storage: Store at 20-25°C (68-77°F) [see USP Controlled Room Temperature]. DO NOT FREEZE.

Rx only.

Printed in USA

Manufactured by DPT Laboratories, San Antonio, TX 78215
Distributed by Suneva Medical Inc., San Diego, CA 92121

MEDGUIDE SECTION

[Tretinoin Cream, USP (Emollient) 0.05%]

FOR TOPICAL USE ON THE FACE ONLY

What is the Most Important Information about Refissa [Tretinoin Cream, USP (Emollient) 0.05%]

Refissa is a serious medication. It does not eliminate wrinkles or repair sundamaged skin. It may help treat fine wrinkles, spotty discoloration, and rough feeling skin, but it does not “cure” these conditions. Refissa should only be used under supervision of your health care provider as part of a broad skin care program. This program should include avoiding direct sunlight (by using protective clothing and sunscreens with a minimum SPF of 15) and using other moisturizing facial creams that do not contain tretinoin.

You should use Refissa only at bedtime. Do not use drying skin care products. Use the smallest amount of Refissa needed and avoid getting it in your eyes, ears, nose or mouth.

WARNING: Do not use Refissa if you are pregnant or attempting to become pregnant. Avoid sunlight and any other medicines that may increase your sensitivity to sunlight (see below).

Refissa has not been studied in people who are over 50 years of age or in people with moderately or darkly pigmented skin.

What is Refissa?

(What can I expect from Refissa?)

Refissa is a serious medication that may help treat but will not “cure” fine wrinkles, spotty skin discoloration, and rough feeling skin.

Studies show that after 24 weeks, about 30% of the people who used Tretinoin Cream, USP (Emollient) 0.05% for fine wrinkles or spotty discoloration had moderate improvement, another 35% had minimal improvement and 35% had no improvement. About 16% of the people who used Tretinoin Cream, USP (Emollient) 0.05% for rough skin had moderate improvement, 35% had minimal improvement, and 49% had no improvement. There is no evidence that Refissa treats coarse skin, deep wrinkles, yellowing skin, or other skin care problems.

Refissa should be used as part of a broad skin care program. This program should include avoiding direct sunlight (by using protective clothing and sunscreens with a minimum SPF of 15) and using other moisturizing facial creams that do not contain tretinoin. Many people can achieve desired effects by using this program without using Refissa. You should not use Refissa until you have tried a broad skin treatment program without Refissa.

When you use Refissa, improvement in fine wrinkling, spotty skin discoloration and rough skin is not immediate and occurs gradually over time. Generally, you may notice some effects in 3 to 4 months. The effects are usually most noticeable at about 6 months with little additional improvement after that time. If Refissa is stopped, the improvement will gradually diminish.

The safety of using Refissa daily for more than 48 weeks has not been established.

Who Should Not Use Refissa?

You should not use Refissa if you are sunburned or highly sensitive to the sun, if you have eczema, or if your skin is irritated. Refissa can cause increased skin irritation and increased susceptibility to sunburn.

Since Refissa may make your skin more sensitive to sunlight, you should tell your health care professional if you are also using other medicines that increase sensitivity to sunlight because you should not be using Refissa with these medicines. These include but are not limited to: thiazides (used to treat high blood pressure), tetracyclines, fluoroquinolones or sulfonamides (used to treat infection), and phenothiazines (used to treat serious emotional problems). If you are taking any prescription medicines, non-prescription medicines or using any facial creams, check with a health care professional to make sure they do not interact with Refissa.

Pregnancy Warning: Safe use during pregnancy has not been shown. There are reports of birth defects with laboratory animals and humans that were given tretinoin by mouth. You should not use Refissa [Tretinoin Cream, USP (Emollient) 0.05%] if you are pregnant or trying to become pregnant.

It is not known if Refissa is passed to infants through breast milk. Safe use in children has not been shown.

The safety and effectiveness of Refissa for people over age 50 or with darker skin coloration has not been proven.

How should I use Refissa?

You should apply Refissa to your face once a day before retiring using only enough to cover the entire affected area lightly. Gently wash your face with a mild soap, pat the skin dry, and wait 20 to 30 minutes before applying Refissa. Apply a pea-sized amount of cream to cover your entire face. You may feel a warmth or slight stinging when Refissa is first applied.

You must be especially careful when applying the cream to avoid your eyes, ears, nostrils, or mouth. Refissa may cause severe redness, itching, burning, stinging, and peeling if applied to these areas.

Using larger than necessary amounts of Refissa will not speed results and can cause an overdose. An overdose can result in red and peeling skin as well as some pain or discomfort.

You may use cosmetics after applying Refissa. Make sure to clean your face thoroughly before applying Refissa again.

What should I avoid while using Refissa?

Refissa increases your sensitivity to sunlight. Avoid sunlight as much as possible. Use protective clothing and a sunscreen with a minimum SPF of 15. Do not sunbathe or use sunlamps. If you are sensitive to sunlight or have a job that requires you to be out in the sun for long periods, you must use extreme caution.

While using Refissa, avoid any products that can dry or irritate the skin. For example, avoid products applied to the skin that contain alcohol, spices, or lime. Also, avoid cleansers, hair removal, or other products that can irritate the skin.

What Are the Possible Side Effects of Refissa?

The most common side effects are skin reactions. Itching, red, and dry skin have been reported. So have burning, stinging, and peeling skin. These are most often mild and are most common when treatment is started.

How Can I Get Additional Information?

This leaflet summarizes the most important information about Refissa. If you would like more information, talk to your doctor or other health care provider. There is also a leaflet written for health professionals that your pharmacist can provide for you.

CALL YOUR DOCTOR FOR MEDICAL ADVICE ABOUT SIDE EFFECTS. YOU ARE ENCOURAGED TO REPORT NEGATIVE SIDE EFFECTS OF PRESCRIPTION DRUGS TO THE FDA. VISIT WWW.FDA.GOV/MEDWATCH, OR CALL 1-800-FDA-1088.

Suneva Medical Inc.
San Diego, CA 92121

PACKAGE LABEL. PRINCIPAL DISPLAY PANEL - 40g carton label

NDC 50224-002-03

Refissa
Tretinoin Cream, USP(Emollient) 0.05 %

Rx Only NET WT 40 g

Tretinoin-40g

PACKAGE LABEL. PRINCIPAL DISPLAY PANEL - 20g carton label

NDC 50224-002-06

Refissa
Tretinoin Cream, USP(Emollient) 0.05 %

Rx Only NET WT 20 g

Tretinoin-20g

PACKAGE LABEL. PRINCIPAL DISPLAY PANEL - Obagi Medical 20g carton label

NDC 50224-002-02

Refissa
Tretinoin Cream, USP(Emollient) 0.05 %

Rx Only NET WT 20 g

Obagi-Medical-20g